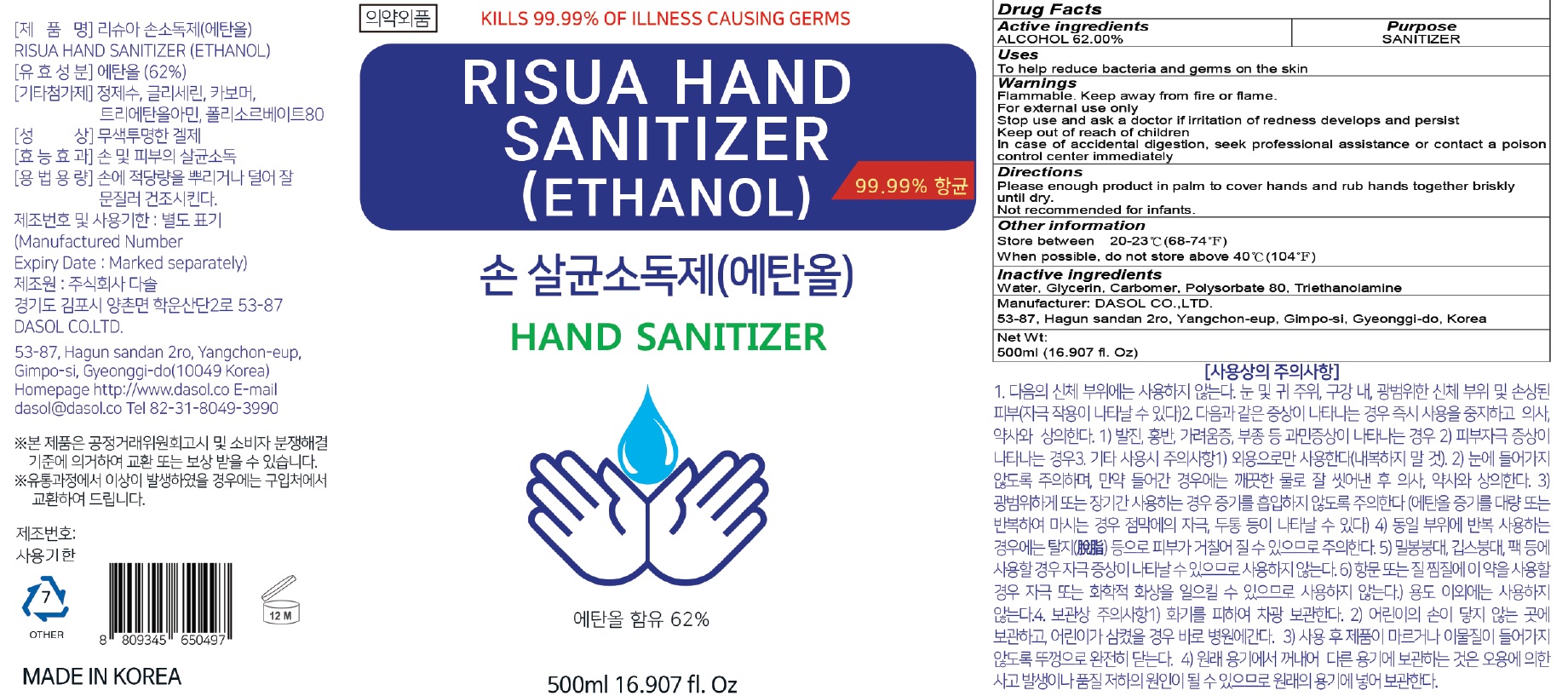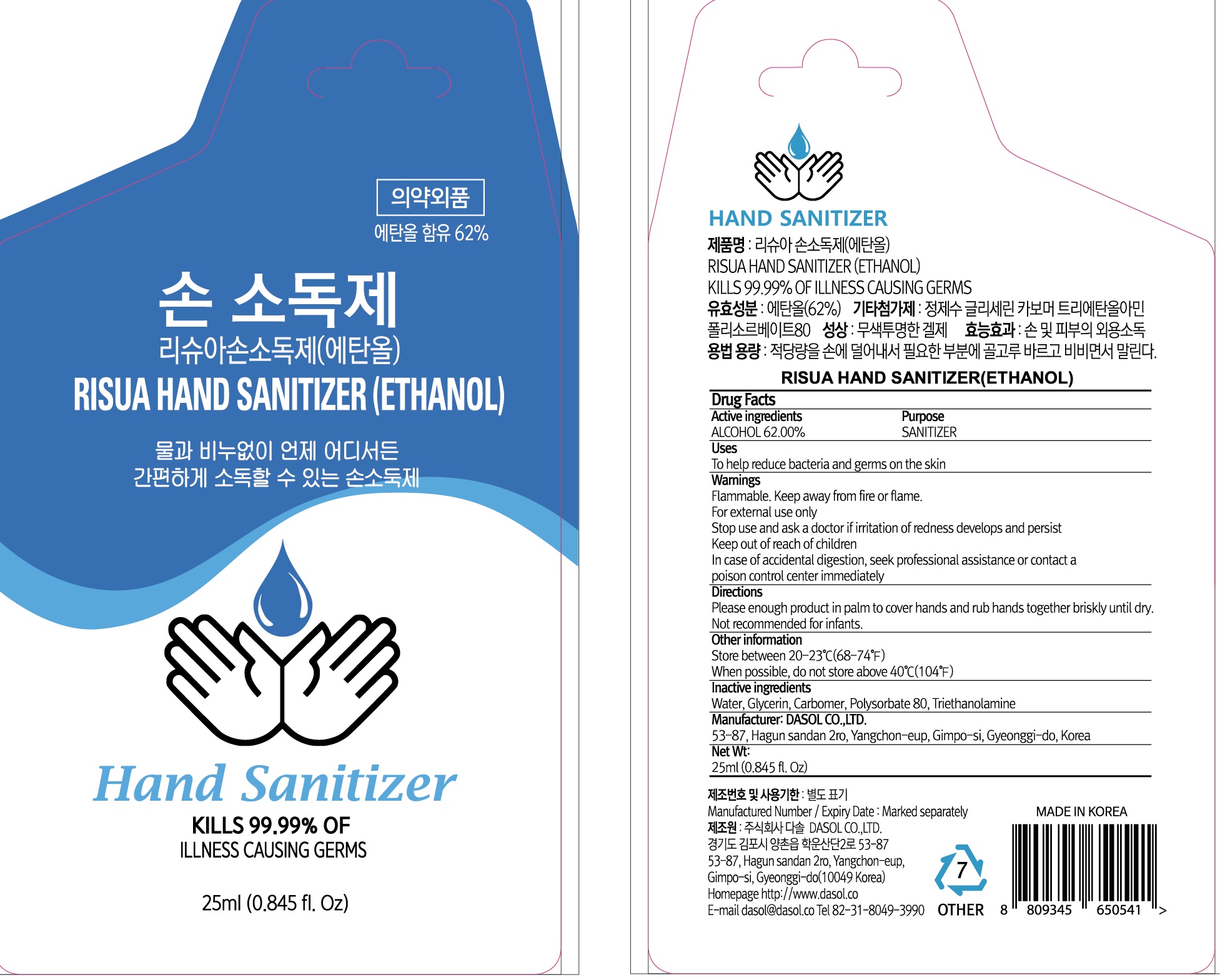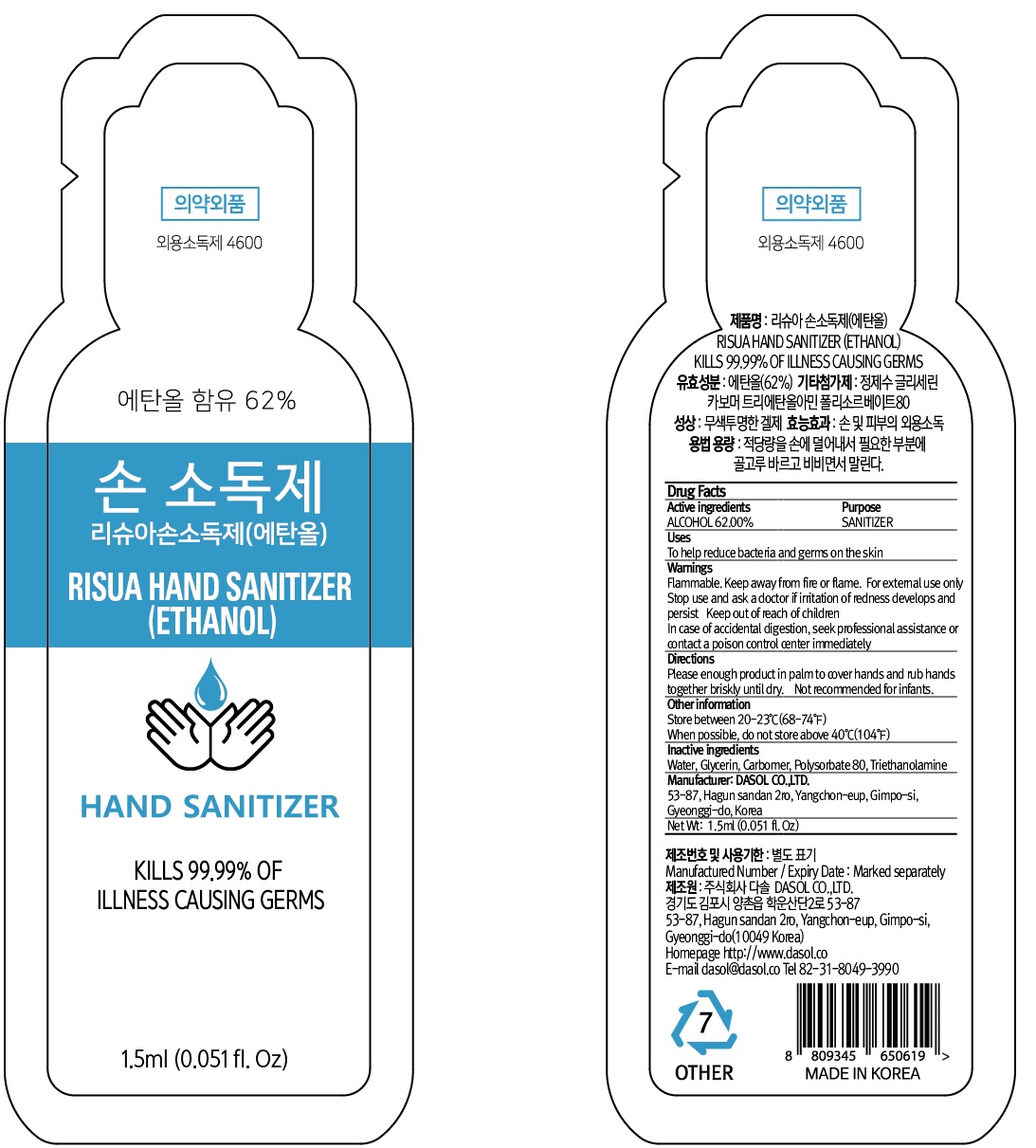 DRUG LABEL: RISUA HAND SANITIZER ETHANOL
NDC: 73758-010 | Form: GEL
Manufacturer: Dasol Co.,ltd.
Category: otc | Type: HUMAN OTC DRUG LABEL
Date: 20200327

ACTIVE INGREDIENTS: ALCOHOL 62.0 g/100 mL
INACTIVE INGREDIENTS: Water; Glycerin; CARBOMER HOMOPOLYMER, UNSPECIFIED TYPE; Polysorbate 80; TROLAMINE

Active Ingredients

Active ingredients: ALCOHOL 62.00%

INACTIVE INGREDIENT

Inactive ingredients:

Water, Glycerin, Carbomer, Polysorbate 80, Triethanolamine

Purpose

Purpose: SANITIZER

Warnings

Flammable. Keep away from fire or flame.
For external use only
Stop use and ask a doctor if irritation of redness develops and persist
Keep out of reach of children
In case of accidental digestion, seek professional assistance or contact a poison control center immediately

KEEP OUT OF REACH OF CHILDREN

Uses

To help remove bacteria and germs on the skin

Directions

Please enough product in palm to cover hands and rub hands together briskly until dry.
Not recommended for infants.